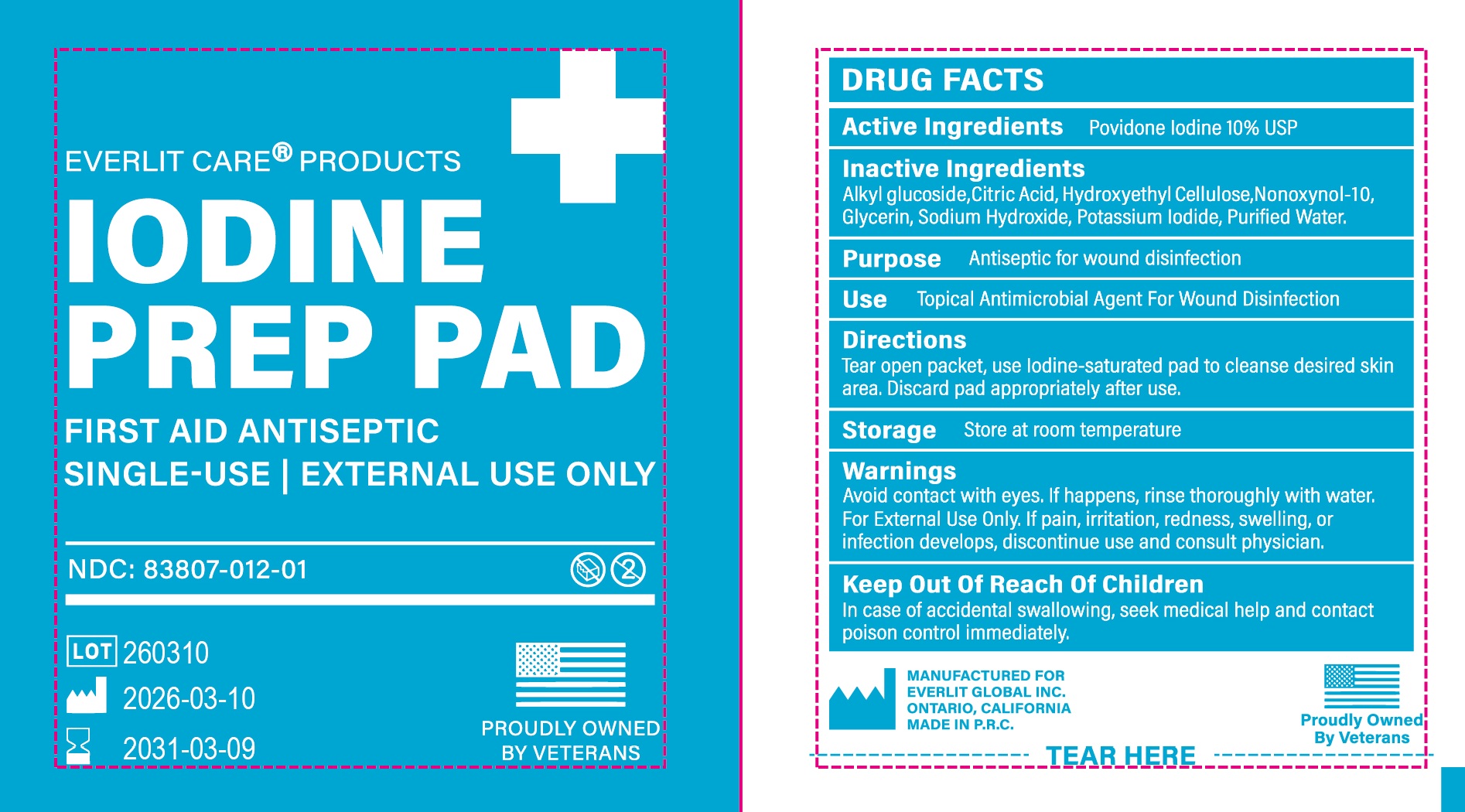 DRUG LABEL: EVERLIT CARE PRODUCTS IODINE PREP PAD
NDC: 83807-012 | Form: CLOTH
Manufacturer: EVERLIT GLOBAL INC.
Category: otc | Type: HUMAN OTC DRUG LABEL
Date: 20260209

ACTIVE INGREDIENTS: POVIDONE-IODINE 0.54 g/1 1
INACTIVE INGREDIENTS: WATER; NONOXYNOL-10; CITRIC ACID; HYDROXYETHYL CELLULOSE (100 MPA.S AT 2%); GLYCERIN; SODIUM HYDROXIDE; POTASSIUM IODIDE; C12-20 ALKYL GLUCOSIDE

83807-012, Everlit Care Products Iodine Prep Pad

Active Ingredient

Povidone Iodine USP 10%

Purpose

Antiseptic for wound disinfection

Uses

Topical antimicrobial agent for wound disinfection

Warnings

Avoid contact with eyes. If happens, rinse thoroughly with water

For External Use Only.

If pain, redness, swelling, or infection develops, discontinue use and consult a phsician

Keep out of reach of children

In case of accidental swallowing, seek medical help and contact a Poison Control Center immediately

Other Information

Store at room temperature

Inactive Ingredients

Citric acid, Alkyl Glucoside, Hydroxyethyl cellulose, Nonoxynol-9, Glycerin, Soidium hydroxide, Potassium iodine, Purified water

Directions

Tear open the packet, use iodine saturated pad to cleanse desired skin area. Discard pad appropriately after use.